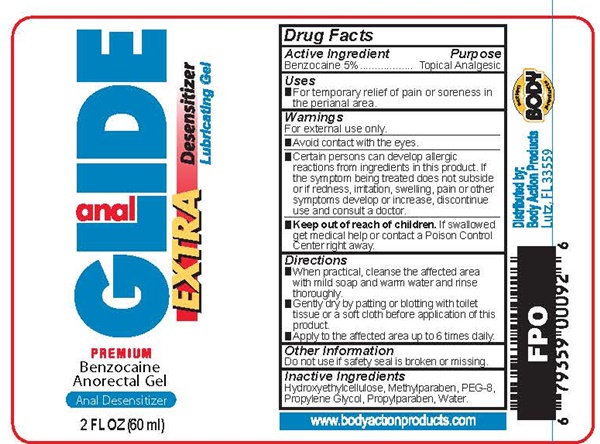 DRUG LABEL: anal GLIDE
NDC: 70742-092 | Form: GEL
Manufacturer: Product Max Group Inc
Category: otc | Type: HUMAN OTC DRUG LABEL
Date: 20160808

ACTIVE INGREDIENTS: BENZOCAINE 2833 mg/60 mL
INACTIVE INGREDIENTS: HYDROXYETHYL CELLULOSE (140 MPA.S AT 5%); METHYLPARABEN; POLYETHYLENE GLYCOL 400; PROPYLENE GLYCOL; PROPYLPARABEN; WATER

anal GLIDE - 092

Drug Facts Active Ingredient

Benzocaine 5%

Purpose

Topical Analgesic

Keep out of reach of children

If swallowed get medical help or contact a Poison Control Center right away.

Uses

- For temporary relief of pain or soreness in the perianal area.

Warnings

For external use only.

- Avoid contact with eyes.
- Certain persons can develop allergic reactions from ingredients in this product. If the symptom being treated goes not subside or if redness, irritation, swelling, pain or other symptoms develop or increase, discontinue use and consult a doctor.

Directions

- When practical, cleanse the affected area with mild soap and warm water and rinse thoroughly.
- Gently dry by patting or blotting with toilet tissue or a soft cloth before application of this product.
- Apply to the affected area up to 6 times daily.

Other Information

Do not use if safety seal is broken or missing.

Inactive Ingredients

Hydroxyethylcellulose, Methylparaben, PEG-8, Propylene Glycol, Propylparaben, Water

anal GLIDE EXTRA product label

anal GLIDE EXTRA

Desensitizer Lubricating Gel

PREMIUM

Benzocaine Anorectal Gel

Anal Desensitizer

2 FL OZ (60 ml)

www.bodyactionproducts.com

Distributed by:

Body Action Products

Lutz, FL 33559

ACTION BODY PRODUCTS